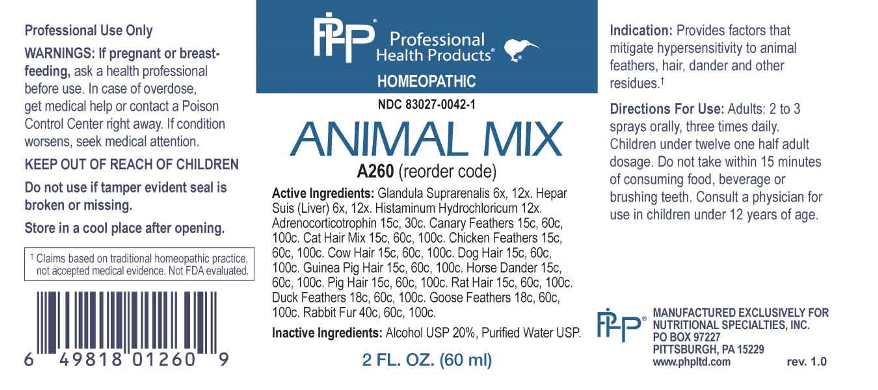 DRUG LABEL: Animal Mix
NDC: 83027-0042 | Form: SPRAY
Manufacturer: Nutritional Specialties, Inc.
Category: homeopathic | Type: HUMAN OTC DRUG LABEL
Date: 20230220

ACTIVE INGREDIENTS: BOS TAURUS ADRENAL GLAND 6 [hp_X]/1 mL; PORK LIVER 6 [hp_X]/1 mL; HISTAMINE DIHYDROCHLORIDE 12 [hp_X]/1 mL; CORTICOTROPIN 15 [hp_C]/1 mL; SERINUS CANARIA FEATHER 15 [hp_C]/1 mL; FELIS CATUS HAIR 15 [hp_C]/1 mL; GALLUS GALLUS FEATHER 15 [hp_C]/1 mL; BOS TAURUS HAIR 15 [hp_C]/1 mL; CANIS LUPUS FAMILIARIS HAIR 15 [hp_C]/1 mL; CAVIA PORCELLUS HAIR 15 [hp_C]/1 mL; EQUUS CABALLUS DANDER 15 [hp_C]/1 mL; SUS SCROFA HAIR 15 [hp_C]/1 mL; RATTUS NORVEGICUS HAIR 15 [hp_C]/1 mL; ANAS PLATYRHYNCHOS FEATHER 18 [hp_C]/1 mL; ANSER ANSER FEATHER 18 [hp_C]/1 mL; ORYCTOLAGUS CUNICULUS HAIR 40 [hp_C]/1 mL
INACTIVE INGREDIENTS: WATER; ALCOHOL

DRUG FACTS:

ACTIVE INGREDIENTS:

Glandula Suprarenalis (Bovine) 6X, 12X, Hepar Suis 6X, 12X, Histaminum Hydrochloricum 12X, Adrenocorticotrophin 15C, 30C, Canary Feathers 15C, 60C, 100C, Cat Hair Mix 15C, 60C, 100C, Chicken Feathers 15C, 60C, 100C, Cow Hair 15C, 60C, 100C, Dog Hair 15C, 60C, 100C, Guinea Pig Hair 15C, 60C, 100C, Horse Dander 15C, 60C, 100C, Pig Hair 15C, 60C, 100C, Rat Hair 15C, 60C, 100C, Duck Feathers 18C, 60C, 100C, Goose Feathers 18C, 60C, 100C, Rabbit Fur 40C, 60C, 100C.

PURPOSE:

Provides factors that mitigate hypersensitivity to animal feathers, hair, dander and other residues.†

†Claims based on traditional homeopathic practice, not accepted medical evidence. Not FDA evaluated.

WARNINGS:

Professional Use Only

If pregnant or breast-feeding, ask a health professional before use.

In case of overdose, get medical help or contact a Poison Control Center right away.

If condition worsens, seek medical attention.

KEEP OUT OF REACH OF CHILDREN

Do not use if tamper evident seal is broken or missing.

Store in a cool place after opening

KEEP OUT OF REACH OF CHILDREN:

In case of overdose, get medical help or contact a Poison Control Center right away.

DIRECTIONS:

Adults: 2 to 3 sprays orally, three times daily. Children under twelve one half adult dosage. Do not take within 15 minutes of consuming food, beverage or brushing teeth. Consult a physician for use in children under 12 years of age.

INDICATIONS:

Provides factors that mitigate hypersensitivity to animal feathers, hair, dander and other residues.†

†Claims based on traditional homeopathic practice, not accepted medical evidence. Not FDA evaluated.

INACTIVE INGREDIENTS:

Alcohol USP 20%, Purified Water USP.

QUESTIONS:

MANUFACTURED EXCLUSIVELY FOR

NUTRITIONAL SPECIALTIES, INC.

PO BOX 97227

PITTSBURG, PA 15229

www.phpltd.com

PACKAGE LABEL DISPLAY:

Professional

Health Products

HOMEOPATHIC

NDC 83027-0042-1

ANIMAL MIX

2 FL. OZ (60 ml)